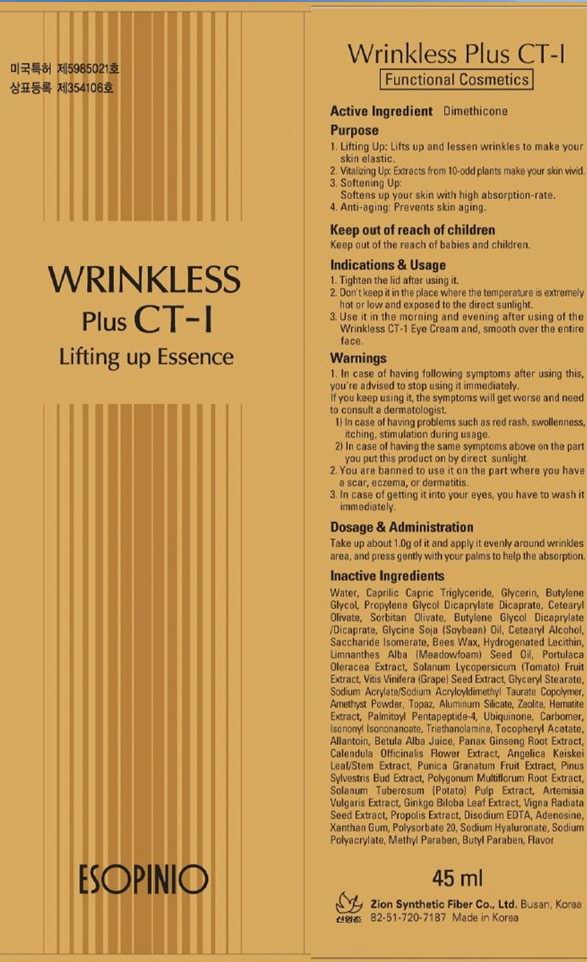 DRUG LABEL: WRINKLESS PLUS
NDC: 44781-120 | Form: CREAM
Manufacturer: ZION SYNTHETIC FIBER CO., LTD.
Category: otc | Type: HUMAN OTC DRUG LABEL
Date: 20110829

ACTIVE INGREDIENTS: DIMETHICONE 0.45 mL/45 mL
INACTIVE INGREDIENTS: Water; Glycerin; Butylene Glycol; PROPYLENE GLYCOL; SOYBEAN OIL; CETOSTEARYL ALCOHOL; MEADOWFOAM SEED OIL; TOMATO; WINE GRAPE; GLYCERYL MONOSTEARATE; ALUMINUM SILICATE; UBIDECARENONE; CARBOMER 934; TROLAMINE; ALLANTOIN; CALENDULA OFFICINALIS FLOWERING TOP; POTATO; ARTEMISIA VULGARIS POLLEN; POLYSORBATE 20; HYALURONATE SODIUM; METHYLPARABEN; BUTYLPARABEN

Drug Facts

Active ingredient: DIMETHICONE

Inactive ingredients:

Water, Caprilic Capric Triglyceride, Glycerin, Butylene Glycol, Propylene Glycol Dicaprylate Dicaprate, Cetearyl Olivate, Sorbitan Olivate, Butylene Glycol Dicaprylate/Dicaprate, Glycine Soja (Soybean) Oil, Cetearyl Alcohol, Saccharide Isomerate, Bees Wax, Hydrogenated Lecithin, Limnanthes Alba (Meadowfoam) Seed Oil, Portulaca Oleracea Extract, Solanum Lycopersicum (Tomato)Fruit Extract, Vitis Vinifera(Grape) Seed Extract, Glyceryl Stearate, Sodium Acrylate/Sodium Acryloyldimethyl Taurate Copolymer, Amethyst Powder, Topaz, Aluminum Silicate, Zeolite, Hematite Extract, Palmitoyl Pentapeptide-4, Ubiquinone, Carbomer, Isononyl Isononanoate, Triethanolamine, Tocopheryl Acetate, Allantoin, Betula Alba Juice, Panax Ginseng Root Extract, Calendula Officinalis Flower Extract, Angelica Keiskei Leaf/Stem Extract, Punica Granatum Fruit Extract, Pinus Sylvestris Bud Extract, Polygonum Multiflorum Root Extract, Solanum Tuberosum (Potato) Pulp Extract, Artemisia Vulgaris Extract,
Ginkgo Biloba Leaf Extract, Vigna Radiata Seed Extract, Propolis Extract, Disodium EDTA, Adenosine, Xanthan Gum, Polysorbate 20, Sodium Hyaluronate, Sodium Polyacrylate, Methyl Paraben, Butyl Paraben, Flavor

Purpose:
Lifting Up - Lifts up and lessen wrinkles to make your skin elastic.
Vitalizing Up - Extracts from 10-odd plants make your skin vivid.
Softening Up - Softens up your skin with high absorption-rate.
Anti-aging - Prevents skin aging.

Warnings:
In case of having following symptoms after using this, you're advised to stop using it immediately. If you keep using it, the symptoms will get worse and need to consult a dermatologist.
- In case of having problems such as red rash, swollenness, itching, stimulation during usage.
- In case of having the same symptoms above on the part you put this product on by direct sunlight.
You are banned to use it on the part where you have a scar, eczema, or dermatitis.
In case of getting it into your eyes, you have to wash it immediately.

Keep out of reach of children:

Keep out of the reach of babies and children.

Indications and Usage:
Tighten the lid after using it.
Don't keep it in the place where the temperature is extremely hot or low and exposed the direct sunlight.
Please apply it an adequate quantity evenly on face, throat, arms and legs at the last stage of basic makeup.
Please apply it once again on your skin at the time when you're going out, sports activity, and any activities of outside.

Dosage and Administration:
Take up about 1.2g - 1.5g of it and smooth over the entire face.